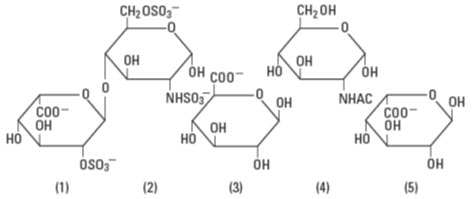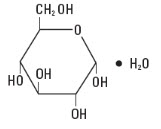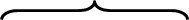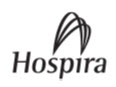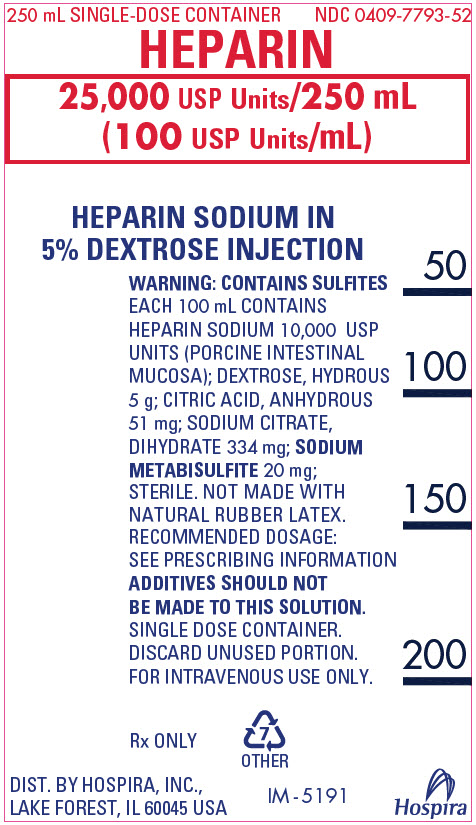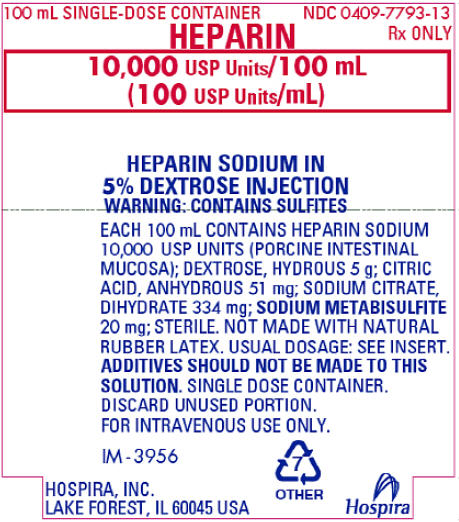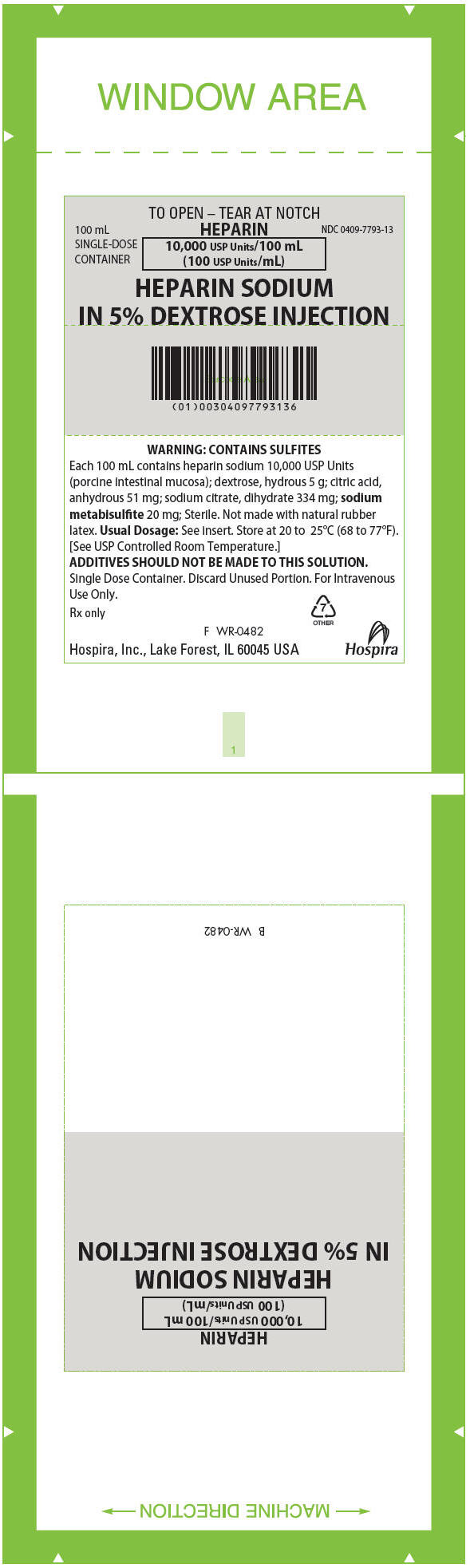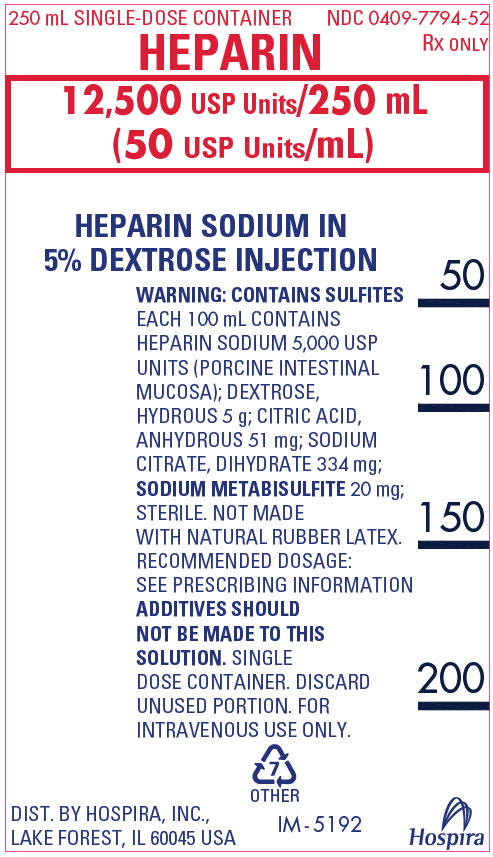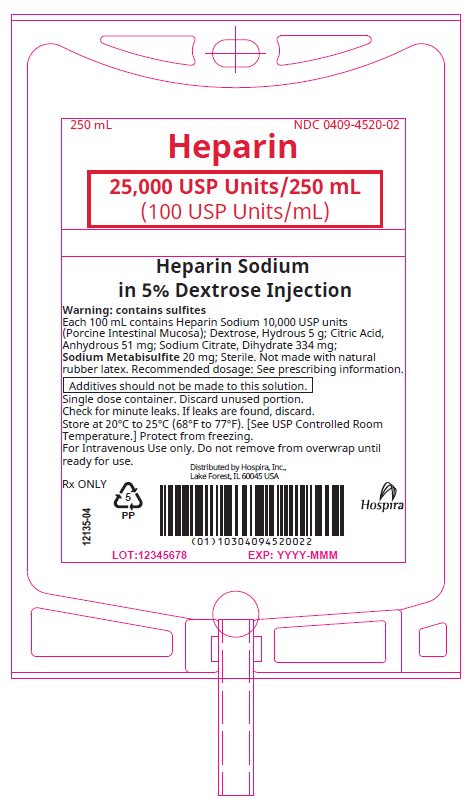 DRUG LABEL: Heparin Sodium and Dextrose
NDC: 0409-7793 | Form: INJECTION, SOLUTION
Manufacturer: Hospira, Inc.
Category: prescription | Type: HUMAN PRESCRIPTION DRUG LABEL
Date: 20251114

ACTIVE INGREDIENTS: HEPARIN SODIUM 10000 [USP'U]/100 mL
INACTIVE INGREDIENTS: DEXTROSE MONOHYDRATE 5 g/100 mL; ANHYDROUS CITRIC ACID 51 mg/100 mL; TRISODIUM CITRATE DIHYDRATE 334 mg/100 mL; SODIUM METABISULFITE 20 mg/100 mL

HIGHLIGHTS OF PRESCRIBING INFORMATION

These highlights do not include all the information needed to use HEPARIN SODIUM IN 5% DEXTROSE INJECTION safely and effectively. See full prescribing information for HEPARIN SODIUM IN 5% DEXTROSE INJECTION.
HEPARIN SODIUM IN 5% DEXTROSE INJECTION, for intravenous use
Initial U.S. Approval: 1939

RECENT MAJOR CHANGES

Contraindications (4) | 12/2023
Warnings and Precautions, Hemorrhage (5.2) | 12/2023
Warnings and Precautions, Heparin-Induced Thrombocytopenia (HIT) and Heparin-Induced Thrombocytopenia and Thrombosis (HITT) (5.3) | 12/2023
Warnings and Precautions, Hypersensitivity Reactions (5.7) | 12/2023
Warnings and Precautions, Hyperkalemia (5.8) | 12/2023
Warnings and Precautions, Elevations of Serum Aminotransferases (5.9) | 12/2023

1 INDICATIONS AND USAGE

Heparin Sodium in 5% Dextrose Injection is indicated for: (1)

- Prophylaxis and treatment of venous thrombosis and pulmonary embolism.
- Prophylaxis and treatment of thromboembolic complications associated with atrial fibrillation.
- Treatment of acute and chronic consumption coagulopathies (disseminated intravascular coagulation).
- Prevention of clotting in arterial and cardiac surgery.
- Prophylaxis and treatment of peripheral arterial embolism.
- Anticoagulant use in blood transfusions, extracorporeal circulation, and dialysis procedures.

2 DOSAGE AND ADMINISTRATION

Recommended Adult Dosages:

- Therapeutic Anticoagulant Effect with Full-Dose Heparin* (2.3)

Intermittent Intravenous Injection | Initial Dose | 10,000 Units, either undiluted or in 50 to 100 mL of 5% Dextrose Injection
Intermittent Intravenous Injection | Subsequent Doses | 5,000 to 10,000 Units every 4 to 6 hours, either undiluted or in 50 to 100 mL of 5% Dextrose Injection
Continuous Intravenous Infusion | Initial Dose | 5,000 Units by intravenous injection
Continuous Intravenous Infusion | Continuous | 20,000 to 40,000 Units every 24 hours in 1000 mL of 5% Dextrose Injection

*Based on 150 lb. (68 kg) patient.

- Cardiovascular Surgery (2.5)

Intravascular via Total Body Perfusion | Initial Dose | Greater than or equal to 150 units/kg; adjust for longer procedures

- Extracorporeal Dialysis (2.8)

Intravascular via Extracorporeal Dialysis | Follow equipment manufacturer's operating directions carefully.
For pediatric dosing see section 2.4 of full prescribing information.

3 DOSAGE FORMS AND STRENGTHS

- Heparin Sodium 25,000 USP units per 250 mL (100 USP units per mL) in 5% Dextrose Injection. (3)
- Heparin Sodium 10,000 USP units per 100 mL (100 USP units per mL) in 5% Dextrose Injection. (3)
- Heparin Sodium 12,500 USP units per 250 mL (50 USP units per mL) in 5% Dextrose Injection. (3)

4 CONTRAINDICATIONS

- History of heparin-induced thrombocytopenia (HIT) or heparin-induced thrombocytopenia and thrombosis (HITT). (4)
- Known hypersensitivity to heparin or pork products. (4)
- In whom suitable blood coagulation tests cannot be performed at appropriate intervals. (4)
- Uncontrollable active bleeding state, except when this is due to disseminated intravascular coagulation. (4)

5 WARNINGS AND PRECAUTIONS

- Fatal Medication Errors: Confirm choice of correct strength prior to administration. (5.1)
- Hemorrhage: Fatal cases have occurred. Monitor for signs of bleeding and manage promptly. (5.2)
- HIT or HITT: Monitor for signs and symptoms and discontinue if indicative of HIT or HITT. (5.3)
- Thrombocytopenia: Monitor platelet count during therapy; discontinue heparin if HIT or HITT is suspected. (5.4)
- Monitoring: Blood coagulation tests guide therapy for full-dose heparin. Monitor platelet count and hematocrit in all patients receiving heparin. (5.5)
- Heparin Resistance: Increased resistance to heparin is frequently encountered in fever, thrombosis, thrombophlebitis, infections with thrombosing tendencies, myocardial infarction, cancer and in postsurgical patients. (5.6)
- Hypersensitivity Reactions: Use in patients with prior reactions only in life-threatening situations. (5.7)
- Hyperkalemia: Measure plasma potassium in patients at risk of hyperkalemia before starting heparin therapy and periodically in all patients. (5.8)
- Elevations of Serum Aminotransferases: Interpret elevation of these enzymes with caution. (5.9)

6 ADVERSE REACTIONS

Most common adverse reactions are: hemorrhage, thrombocytopenia, HIT or HITT, heparin resistance, hypersensitivity reactions, hyperkalemia, and elevations of aminotransferase levels. (6)

To report SUSPECTED ADVERSE REACTIONS, contact Pfizer Inc at 1-800-438-1985 or FDA at 1-800-FDA-1088 or www.fda.gov/medwatch.

7 DRUG INTERACTIONS

Drugs that interfere with coagulation, platelet aggregation or drugs that counteract coagulation may induce bleeding. (7)

FULL PRESCRIBING INFORMATION

1 INDICATIONS AND USAGE

Heparin Sodium in 5% Dextrose Injection is indicated for:

- Prophylaxis and treatment of venous thrombosis and pulmonary embolism
- Prophylaxis and treatment of thromboembolic complications associated with atrial fibrillation
- Treatment of acute and chronic consumption coagulopathies (disseminated intravascular coagulation)
- Prevention of clotting in arterial and cardiac surgery
- Prophylaxis and treatment of peripheral arterial embolism
- Anticoagulant use in blood transfusions, extracorporeal circulation, and dialysis procedures.

2 DOSAGE AND ADMINISTRATION

2.1 Preparation for Administration

Confirm the selection of the correct formulation and strength prior to administration of the drug.

This product should be administered by intravenous infusion.

Do not use Heparin Sodium in 5% Dextrose Injection as a “catheter lock flush” product.

Do not admix with other drugs.

Discard unused portion.

Do not use plastic containers in series connection.

This product should not be infused under pressure.

Parenteral drug products should be inspected visually for particulate matter and discoloration prior to administration, whenever solution and container permit. Use only if solution is clear and container and seals are intact.

To Open
Tear outer wrap and remove solution container.

(Use aseptic technique)

1. Close flow control clamp of administration set.
2. Remove cover from outlet port at bottom of container.
3. Insert piercing pin of administration set into port with a twisting motion until the set is firmly seated.
  NOTE: See full directions on administration set carton.
4. Suspend container from hanger.
5. Squeeze and release drip chamber to establish proper fluid level in chamber.
6. Open flow control clamp and clear air from set. Close clamp.
7. Attach set to venipuncture device. If device is not indwelling, prime and make venipuncture.
8. Regulate rate of administration with flow control clamp.

Warning: Do not use flexible container in series connections.

2.2 Laboratory Monitoring for Efficacy and Safety

Adjust the dosage of heparin sodium according to the patient's coagulation test results. When heparin is given by continuous intravenous infusion, determine the coagulation time approximately every 4 hours in the early stages of treatment. When the drug is administered intermittently by intravenous injection, perform coagulation tests before each injection during the early stages of treatment and at appropriate intervals thereafter. Dosage is considered adequate when the activated partial thromboplastin time (APTT) is 1.5 to 2 times the normal or when the whole blood clotting time is elevated approximately 2.5 to 3 times the control value.

Periodic platelet counts, hematocrits, and tests for occult blood in stool are recommended during the entire course of heparin therapy.

2.3 Therapeutic Anticoagulant Effect with Full-Dose Heparin

The dosing recommendations in Table 1 are based on clinical experience. Although dosage must be adjusted for the individual patient according to the results of suitable laboratory tests, the following dosage schedules may be used as guidelines:

Table 1: Recommended Adult Full-Dose Heparin Regimens for Therapeutic Anticoagulant Effect
Method of Administration | Frequency | Recommended Dose [Based on 150 lb. (68 kg) patient.]
Intermittent Intravenous Injection | Initial Dose | 10,000 Units, either undiluted or in 50 to 100 mL of 5% Dextrose Injection
Intermittent Intravenous Injection | Subsequent Doses | 5,000 to 10,000 Units every 4 to 6 hours, either undiluted or in 50 to 100 mL of 5% Dextrose Injection
Continuous Intravenous Infusion | Initial Dose | 5,000 Units by intravenous injection
Continuous Intravenous Infusion | Continuous | 20,000 to 40,000 Units every 24 hours in 1,000 mL of 5% Dextrose Injection

2.4 Pediatric Use

There are no adequate and well-controlled studies on heparin use in pediatric patients. Pediatric dosing recommendations are based on clinical experience. In general, the following dosage schedule may be used as a guideline in pediatric patients:

Initial Dose | 75 units/kg to 100 units/kg (intravenous bolus over 10 minutes)
Maintenance Dose | Infants: 25 units/kg/hour to 30 units/kg/hour; Infants < 2 months have the highest requirements (average 28 units/kg/hour) Children > 1 year of age: 18 units/kg/hour to 20 units/kg/hour; Older children may require less heparin, similar to weight-adjusted adult dosage
Monitoring | Adjust heparin to maintain APTT of 60 to 85 seconds, assuming this reflects an anti-Factor Xa level of 0.35 to 0.70.

2.5 Cardiovascular Surgery

Patients undergoing total body perfusion for open-heart surgery should receive an initial dose of not less than 150 units of heparin sodium per kilogram of body weight. Frequently, a dose of 300 units per kilogram is used for procedures estimated to last less than 60 minutes or 400 units per kilogram for those estimated to last longer than 60 minutes.

2.6 Converting to Warfarin

To ensure continuous anticoagulation when converting from heparin sodium to warfarin, continue full heparin therapy for several days until the INR (prothrombin time) has reached a stable therapeutic range. Heparin therapy may then be discontinued without tapering [see Drug Interactions (7.1)].

2.7 Converting to Oral Anticoagulants other than Warfarin

For patients currently receiving intravenous heparin, stop intravenous infusion of heparin sodium immediately after administering the first dose of oral anticoagulant; or for intermittent intravenous administration of heparin sodium, start oral anticoagulant 0 to 2 hours before the time that the next dose of heparin was to have been administered.

2.8 Extracorporeal Dialysis

Follow equipment manufacturer's operating directions carefully. A dose of 25 to 30 units/kg followed by an infusion rate of 1,500 to 2,000 units/hour is suggested based on pharmacodynamic data if specific manufacturers' recommendations are not available.

3 DOSAGE FORMS AND STRENGTHS

Heparin Sodium in 5% Dextrose Injection is available as:

- Heparin Sodium 25,000 USP units per 250 mL (100 USP units per mL) in 5% Dextrose Injection.
- Heparin Sodium 10,000 USP units per 100 mL (100 USP units per mL) in 5% Dextrose Injection.
- Heparin Sodium 12,500 USP units per 250 mL (50 USP units per mL) in 5% Dextrose Injection.

4 CONTRAINDICATIONS

The use of Heparin Sodium in 5% Dextrose Injection is contraindicated in patients with the following conditions:

- History of heparin-induced thrombocytopenia (HIT) and heparin-induced thrombocytopenia and thrombosis (HITT) [see Warnings and Precautions (5.3)]
- Known hypersensitivity to heparin or pork products (e.g., anaphylactoid reactions) [see Warnings and Precautions (5.7), Adverse Reactions (6.1)]
- In whom suitable blood coagulation tests — e.g., the whole blood clotting time, partial thromboplastin time, etc., — cannot be performed at appropriate intervals (this contraindication refers to full-dose heparin; there is usually no need to monitor coagulation parameters in patients receiving low-dose heparin) [see Warnings and Precautions (5.5)]
- Uncontrollable active bleeding state except when this is due to disseminated intravascular coagulation [see Warnings and Precautions (5.2)].

5 WARNINGS AND PRECAUTIONS

5.1 Fatal Medication Errors

Do not use this product as a "catheter lock flush" product. Heparin is supplied in various strengths. Fatal hemorrhages have occurred due to medication errors. Carefully examine all heparin products to confirm the correct container choice prior to administration of the drug.

5.2 Hemorrhage

Hemorrhage, including fatal events, has occurred in patients receiving heparin sodium. Avoid using heparin in the presence of major bleeding, except when the benefits of heparin therapy outweigh the potential risks.

Hemorrhage can occur at virtually any site in patients receiving heparin. Adrenal hemorrhage (with resultant acute adrenal insufficiency), ovarian hemorrhage, and retroperitoneal hemorrhage have occurred during anticoagulant therapy with heparin [see Adverse Reactions (6.1)]. A higher incidence of bleeding has been reported in patients, particularly women, over 60 years of age [see Clinical Pharmacology (12.3)]. An unexplained fall in hematocrit or fall in blood pressure should lead to serious consideration of a hemorrhagic event.

Use heparin sodium with caution in disease states in which there is increased risk of hemorrhage, including:

- Cardiovascular — Subacute bacterial endocarditis. Severe hypertension.
- Surgical — During and immediately following (a) spinal tap or spinal anesthesia or (b) major surgery, especially involving the brain, spinal cord or eye.
- Hematologic — Conditions associated with increased bleeding tendencies, such as hemophilia, thrombocytopenia and some vascular purpuras.
- Patients with hereditary antithrombin III deficiency receiving concurrent antithrombin III therapy – The anticoagulant effect of heparin is enhanced by concurrent treatment with antithrombin III (human) in patients with hereditary antithrombin III deficiency. To reduce the risk of bleeding, reduce the heparin dose during concomitant treatment with antithrombin III (human).
- Gastrointestinal — Ulcerative lesions and continuous tube drainage of the stomach or small intestine.
- Other — Menstruation, liver disease with impaired hemostasis.

5.3 Heparin-Induced Thrombocytopenia (HIT) and Heparin-Induced Thrombocytopenia and Thrombosis (HITT)

HIT is a serious immune-mediated reaction resulting from irreversible aggregation of platelets. HIT occurs in patients treated with heparin and is due to the development of antibodies to a platelet Factor 4-heparin complex that induce in vivo platelet aggregation. HIT may progress to the development of venous and arterial thromboses, a condition known as HITT. Thrombotic events may also be the initial presentation for HIT. These serious thromboembolic events include deep vein thrombosis, pulmonary embolism, cerebral vein thrombosis, limb ischemia, stroke, myocardial infarction, thrombus formation on a prosthetic cardiac valve, mesenteric thrombosis, renal arterial thrombosis, skin necrosis, gangrene of the extremities that may lead to amputation, and possibly death.

Once HIT or HITT is diagnosed or strongly suspected, discontinue all heparin sources (including heparin flushes) and use an alternative anticoagulant.

Immune-mediated HIT is diagnosed based on clinical findings supplemented by laboratory tests confirming the presence of antibodies to heparin, or platelet activation induced by heparin. Obtain platelet counts at baseline and periodically during heparin administration. A drop in platelet count greater than 50% from baseline is considered indicative of HIT. Platelet counts begin to fall 5 to 10 days after exposure to heparin in heparin-naïve individuals and reach a threshold by days 7 to 14. In contrast, “rapid onset” HIT can occur very quickly (within 24 hours following heparin initiation), especially in patients with a recent exposure to heparin (i.e., previous 3 months).

Thrombosis development shortly after documenting thrombocytopenia is a characteristic finding in almost half of all patients with HIT.

Monitor thrombocytopenia of any degree closely. If the platelet count falls below 100,000/mm^3 or if recurrent thrombosis develops, promptly discontinue heparin, evaluate for HIT and HITT, and, if necessary, administer an alternative anticoagulant.

HIT or HITT can occur up to several weeks after the discontinuation of heparin therapy. Patients presenting with thrombocytopenia or thrombosis after discontinuation of heparin should be evaluated for HIT or HITT.

5.4 Thrombocytopenia

Thrombocytopenia has been reported to occur in patients receiving heparin with a reported incidence of up to 30%. It can occur 2 to 20 days (average 5 to 9) following the onset of heparin therapy. Obtain platelet counts before and periodically during heparin therapy. Monitor thrombocytopenia of any degree closely. If the count falls below 100,000/mm^3 or if recurrent thrombosis develops, promptly discontinue heparin, evaluate for HIT, and, if necessary, administer an alternative anticoagulant [see Warnings and Precautions (5.3)].

5.5 Coagulation Testing and Monitoring

When using a full dose heparin regimen, adjust the heparin dose based on frequent blood coagulation tests. If the coagulation test is unduly prolonged or if hemorrhage occurs, heparin sodium should be discontinued promptly [see Overdosage (10)]. Periodic platelet counts, hematocrits and tests for occult blood in stool are recommended during the entire course of heparin therapy [see Dosage and Administration (2.2)].

5.6 Heparin Resistance

Increased resistance to heparin is frequently encountered in fever, thrombosis, thrombophlebitis, infections with thrombosing tendencies, myocardial infarction, cancer and in postsurgical patients, and patients with antithrombin III deficiency.

Consider measurement of anti-thrombin levels if heparin resistance is suspected. Monitor coagulation tests frequently in such patients. It may be necessary to adjust the dose of heparin based on coagulation test monitoring, such as anti-Factor Xa levels and/or partial thromboplastin time.

5.7 Hypersensitivity Reactions

Hypersensitivity reactions with chills, fever and urticaria as the most usual manifestations and also asthma, rhinitis, lacrimation, and anaphylactoid reactions have been reported. Patients with documented hypersensitivity to heparin should be given the drug only in clearly life-threatening situations [see Adverse Reactions (6.1)].

Because Heparin Sodium in 5% Dextrose Injection is derived from animal tissue, monitor for signs and symptoms of hypersensitivity when it is used in patients with a history of allergy to pork products.

This product contains sodium metabisulfite, a sulfite that may cause allergic-type reactions including anaphylactic symptoms and life-threatening or less severe asthmatic episodes in certain susceptible people. The overall prevalence of sulfite sensitivity in the general population is unknown and probably low. Sulfite sensitivity is seen more frequently in asthmatic than in nonasthmatic people.

5.8 Hyperkalemia

Heparin can suppress adrenal secretion of aldosterone leading to hyperkalemia, particularly in patients with diabetes mellitus, chronic renal failure, pre-existing metabolic acidosis, a raised plasma potassium, or taking potassium sparing drugs. The risk of hyperkalemia appears to increase with duration of therapy but is usually reversible upon discontinuation of heparin.

Measure plasma potassium in patients at risk of hyperkalemia before starting heparin therapy and periodically in all patients treated for more than 5 days or earlier as deemed fit by the clinician.

5.9 Elevations of Serum Aminotransferases

Significant elevations of aspartate aminotransferase (AST) and alanine aminotransferase (ALT) levels have occurred in patients who have received heparin. Elevation of these enzymes in patients receiving heparin should be interpreted with caution. These elevations typically resolve upon heparin discontinuation.

6 ADVERSE REACTIONS

The following serious adverse reactions are described elsewhere in the labeling:

- Hemorrhage [see Warnings and Precautions (5.2)]
- Heparin-Induced Thrombocytopenia and Heparin-Induced Thrombocytopenia with Thrombosis [see Warnings and Precautions (5.3)]
- Thrombocytopenia [see Warnings and Precautions (5.4)]
- Heparin Resistance [see Warnings and Precautions (5.6)]
- Hypersensitivity [see Warnings and Precautions (5.7)]
- Hyperkalemia [see Warnings and Precautions (5.8)]
- Elevations of Serum Aminotransferases [see Warnings and Precautions (5.9)]

6.1 Postmarketing Experience

The following adverse reactions have been identified during post-approval use of heparin sodium. Because these reactions are reported voluntarily from a population of uncertain size, it is not always possible to reliably estimate their frequency.

- Hemorrhage - Hemorrhage is the chief complication that may result from heparin therapy [see Warnings and Precautions (5.2)]. An overly prolonged clotting time or minor bleeding during therapy can usually be controlled by withdrawing the drug [see Overdosage (10)]. Gastrointestinal or urinary tract bleeding during anticoagulant therapy may indicate the presence of an underlying occult lesion. Bleeding can occur at any site but certain specific hemorrhagic complications may be difficult to detect:
  - Adrenal hemorrhage, with resultant acute adrenal insufficiency, has occurred with heparin therapy, including fatal cases.
  - Ovarian (corpus luteum) hemorrhage developed in a number of women of reproductive age receiving short- or long-term anticoagulant therapy.
  - Retroperitoneal hemorrhage.
- Vascular Disorders – Contusion, vasospastic reactions (including episodes of painful, ischemic, and cyanosed limbs).
- HIT and HITT, including delayed onset cases, and Thrombocytopenia - [see Warnings and Precautions (5.3, 5.4)]
- Histamine-like reactions – Such reactions have been observed at the site of injections. Necrosis of the skin has been reported at the site of subcutaneous injection of heparin, occasionally requiring skin grafting.
- Hypersensitivity – Generalized hypersensitivity reactions have been reported with chills, fever, and urticaria as the most usual manifestations, and asthma, rhinitis, lacrimation, headache, nausea and vomiting, and anaphylactoid reactions, including shock, occurring more rarely. Itching and burning, especially on the plantar site of the feet, may occur [see Warnings and Precautions (5.7)].
- Musculoskeletal, Connective Tissue and Bone Disorders – Osteoporosis with long-term administration of heparin.
- Metabolism and Nutrition Disorders – Hyperkalemia.
- General Disorders and Administration Site Conditions – Erythema, mild pain, ulceration.
- Elevations of Serum Aminotransferases – Significant elevations of aspartate aminotransferase (AST) and alanine aminotransferase (ALT) levels have occurred in patients who have received heparin.
- Others – Osteoporosis following long-term administration of high-doses of heparin, cutaneous necrosis after systemic administration, suppression of aldosterone synthesis, delayed transient alopecia, priapism, and rebound hyperlipemia on discontinuation of heparin sodium have also been reported.

7 DRUG INTERACTIONS

7.1 Oral Anticoagulants

Heparin sodium may prolong the one-stage prothrombin time. Therefore, when heparin sodium is given with dicumarol or warfarin sodium, a period of at least 5 hours after the last intravenous dose or 24 hours after the last subcutaneous dose should elapse before blood is drawn if a valid prothrombin time is to be obtained.

7.2 Platelet Inhibitors

Drugs such as NSAIDS (including acetylsalicylic acid, ibuprofen, indomethacin, and celecoxib), dextran, phenylbutazone, thienopyridines, dipyridamole, hydroxychloroquine, glycoprotein IIv/IIa antagonists (including abciximab, eptifibatide, and tirofiban), and others that interfere with platelet-aggregation reactions (the main hemostatic defense of heparinized patients) may induce bleeding and should be used with caution in patients receiving heparin sodium. To reduce the risk of bleeding, a reduction in the dose of antiplatelet agent or heparin is recommended.

7.3 Other Medications that May Interfere with Heparin

Digitalis, tetracyclines, nicotine, antihistamines, or intravenous nitroglycerine may partially counteract the anticoagulant action of heparin sodium. Intravenous nitroglycerin administered to heparinized patients may result in a decrease of the partial thromboplastin time with subsequent rebound effect upon discontinuation of nitroglycerin. Careful monitoring of partial thromboplastin time and adjustment of heparin dosage are recommended during coadministration of heparin and intravenous nitroglycerin. Antithrombin III (human) – The anticoagulant effect of heparin is enhanced by concurrent treatment with antithrombin III (human) in patients with hereditary antithrombin III deficiency. To reduce the risk of bleeding, a reduced dosage of heparin is recommended during treatment with antithrombin III (human).

8 USE IN SPECIFIC POPULATIONS

8.1 Pregnancy

Risk Summary

In published reports, heparin exposure during pregnancy did not show evidence of an increased risk of adverse maternal or fetal outcomes in humans. No teratogenicity was observed in animal reproduction studies with administration of heparin sodium to pregnant rats and rabbits during organogenesis at doses up to 10,000 USP units/kg/day, approximately 10 times the maximum recommended human dose (MRHD) of 40,000 USP units/24 hours infusion [see Data]. In pregnant animals, doses up to 10 times higher than the maximum human daily dose based on body weight resulted in increased resorptions. Consider the benefits and risks of Heparin Sodium in 5% Dextrose Injection to a pregnant woman and possible risks to the fetus when prescribing Heparin Sodium in 5% Dextrose Injection.

The estimated background risk of major birth defects and miscarriage for the indicated population is unknown. In the U.S. general population, the estimated background risk of major birth defects and miscarriage in clinically recognized pregnancies is 2–4% and 15–20%, respectively.

Data

Human Data

The maternal and fetal outcomes associated with uses of heparin via various dosing methods and administration routes during pregnancy have been investigated in numerous studies. These studies generally reported normal deliveries with no maternal or fetal bleeding and no other complications.

Animal Data

In a published study conducted in rats and rabbits, pregnant animals received heparin intravenously during organogenesis at a dose of 10,000 USP units/kg/day, approximately 10 times the maximum human daily dose based on body weight. The number of early resorptions increased in both species. There was no evidence of teratogenic effects.

8.2 Lactation

Risk Summary

There is no information regarding the presence of Heparin Sodium in 5% Dextrose Injection in human milk, the effects on the breastfed infant, or the effects on milk production. Due to its large molecular weight, heparin is not likely to be excreted in human milk, and any heparin in milk would not be orally absorbed by a nursing infant. The developmental and health benefits of breastfeeding should be considered along with the mother's clinical need for Heparin Sodium in 5% Dextrose Injection and any potential adverse effects on the breastfed infant from Heparin Sodium in 5% Dextrose Injection or from the underlying maternal condition [see Use in Specific Populations (8.4)].

8.4 Pediatric Use

There are no adequate and well controlled studies on heparin use in pediatric patients. Pediatric dosing recommendations are based on clinical experience [see Dosage and Administration (2.4)].

8.5 Geriatric Use

There are limited adequate and well-controlled studies in patients 65 years and older. However, a higher incidence of bleeding has been reported in patients over 60 years of age, especially women [see Warnings and Precautions (5.2)]. Lower doses of heparin may be indicated in these patients [see Clinical Pharmacology (12.3)].

10 OVERDOSAGE

An overdose requires immediate medical attention and treatment.

Symptoms

Bleeding is the chief sign of heparin overdosage. Easy bruising, petechial formations, nosebleeds, blood in urine or tarry stools may be the first signs or symptoms of a heparin overdose. In the event of symptomatic heparin overdose, consider stopping heparin infusion.

Treatment

Neutralization of heparin effect:

When clinical circumstances (bleeding) require reversal of heparinization, protamine sulfate (1% solution) by slow infusion will neutralize heparin sodium. No more than 50 mg should be administered, very slowly, in any 10 minute period. Each mg of protamine sulfate neutralizes approximately 100 USP Heparin Units. The amount of protamine required decreases over time as heparin is metabolized. Although the metabolism of heparin is complex, it may, for the purpose of choosing a protamine dose, be assumed to have a half-life of about 30 minutes after intravenous injection.

Ideally, the dose required to neutralize the action of heparin should be guided by blood coagulation tests or calculated from a protamine neutralization test.

Because fatal reactions often resembling anaphylaxis have been reported, protamine sulfate should be given only when resuscitation techniques and treatment of anaphylactoid shock are readily available.

Blood or plasma transfusions may be necessary; these dilute but do not neutralize heparin.

For additional information, consult the prescribing information for Protamine Sulfate Injection, USP.

11 DESCRIPTION

Heparin is a heterogeneous group of straight-chain anionic mucopolysaccharides, called glycosaminoglycans having anticoagulant properties. Although others may be present, the main sugars occurring in heparin are: (1) α-L-iduronic acid 2-sulfate, (2) 2-deoxy-2-sulfamino-α-D-glucose 6∙sulfate, (3) β-D-glucuronic acid, (4) 2-acetamido-2-deoxy-α-D-glucose, and (5) α-L-iduronic acid. These sugars are present in decreasing amounts, usually in the order (2)>(1)>(4)>(3)>(5), and are joined by glycosidic linkages, forming polymers of varying sizes. Heparin is strongly acidic because of its content of covalently linked sulfate and carboxylic acid groups. In heparin sodium, the acidic protons of the sulfate units are partially replaced by sodium ions.

Structure of Heparin Sodium (representative subunits):

Dextrose, USP is chemically designated D-glucose, monohydrate C6H12O6 ∙ H2O, a hexose sugar freely soluble in water. It has the following structural formula:

Water for Injection, USP is chemically designated H2O.

Intravenous solutions with heparin sodium (derived from porcine intestinal mucosa) are sterile, nonpyrogenic fluids for intravenous administration. Each 100 mL contains heparin sodium 5,000 or 10,000 USP Units; dextrose, hydrous 5 g; citric acid, anhydrous, 51 mg and sodium citrate, dihydrate 334 mg added as buffers; sodium metabisulfite 20 mg added as an antioxidant. Each liter contains electrolytes sodium and citrate in amounts as listed in HOW SUPPLIED/STORAGE AND HANDLING Table. See Table for summary of contents and characteristics of this solution. The potency is determined by a biological assay using a USP reference standard based on units of heparin activity per milligram.

The flexible plastic container is fabricated either from a specially formulated nonplasticized, thermoplastic co-polyester (CR3) or from a polyolefin film. Water can permeate from inside the container into the overwrap but not in amounts sufficient to affect the solution significantly. Solutions inside the plastic container also can leach out certain of its chemical components in very small amounts before the expiration period is attained. However, the safety of the plastic has been confirmed by tests in animals according to USP biological standards for plastic containers.

12 CLINICAL PHARMACOLOGY

12.1 Mechanism of Action

Heparin interacts with the naturally occurring plasma protein, antithrombin III, to induce a conformational change, which markedly enhances the serine protease activity of antithrombin III, thereby inhibiting the activated coagulation factors involved in the closing sequence, particularly Xa and IIa. Small amounts of heparin inhibit Factor Xa, and larger amounts inhibit thrombin (Factor IIa). Heparin also prevents the formation of a stable fibrin clot by inhibiting the activation of the fibrin stabilizing factor. Heparin does not have fibrinolytic activity; therefore, it will not lyse existing clots.

12.2 Pharmacodynamics

Various times (activated clotting time, activated partial thromboplastin time, prothrombin time, whole blood clotting time) are prolonged by full therapeutic doses of heparin; in most cases, they are not measurably affected by low doses of heparin. Bleeding time is usually unaffected by heparin.

12.3 Pharmacokinetics

Absorption

Heparin is not absorbed through the gastrointestinal tract and therefore administered via parenteral route. Peak plasma concentration and the onset of action are achieved immediately after intravenous administration.

Distribution

Heparin is highly bound to antithrombin, fibrinogens, globulins, serum proteases and lipoproteins. The volume of distribution is 0.07 L/kg.

Elimination

Metabolism

Heparin does not undergo enzymatic degradation.

Excretion

Heparin is mainly cleared from the circulation by liver and reticuloendothelial cells mediated uptake into extravascular space. Heparin undergoes biphasic clearance, a) rapid saturable clearance (zero order process due to binding to proteins, endothelial cells and macrophages) and b) slower first order elimination. Low doses of heparin are cleared mostly by a saturable, rapid, zero-order process. Slower first order elimination usually occurs with very high doses of heparin and is dependent on renal function. The plasma half-life is dose-dependent, and it ranges from 0.5 to 2 h.

Specific Populations

Geriatric Patients

Patients over 60 years of age, following similar doses of heparin, may have higher plasma levels of heparin and longer activated partial thromboplastin times (APTTs) compared with patients under 60 years of age [see Use in Specific Populations (8.5)].

Renal and Hepatic Impairment

The rate of clearance of unfractionated heparin may be decreased in patients with renal or hepatic impairment. Patients with renal or hepatic impairment, following similar doses of heparin may have higher plasma levels of heparin compared with patients with normal renal and hepatic function [see Warnings and Precautions (5.2)].

13 NONCLINICAL TOXICOLOGY

13.1 Carcinogenesis, Mutagenesis, Impairment of Fertility

Long term studies in animals to evaluate the carcinogenic potential, reproduction studies in animals to determine effects on fertility of males and females, and the studies to determine mutagenic potential have not been conducted.

16 HOW SUPPLIED/STORAGE AND HANDLING

Intravenous solutions with heparin sodium are available in single-dose flexible plastic containers in various sizes and concentrations as shown in the accompanying Table as follows:

 |  | Contents and Characteristics Per 100 mL
Unit of Sale | Concentration | Dextrose (hydrous) | Sodium mEq/L | Citrate mEq/L | Tonicity
NDC 0409-7793-62; Case of 24 Single-dose flexible plastic containers | 25,000 USP Units/250 mL (100 USP Units/mL) | 5 g | 39 | 42 | Isotonic
NDC 0409-4520-30; Case of 30 Single-dose flexible plastic containers | 25,000 USP Units/250 mL (100 USP Units/mL) | 5 g | 39 | 42 | Isotonic
NDC 0409-7793-23; Case of 24 Single-dose flexible plastic containers | 10,000 USP Units/100 mL (100 USP Units/mL) | 5 g | 39 | 42 | Isotonic
NDC 0409-7794-62; Case of 24 Single-dose flexible plastic containers | 12,500 USP Units/250 mL (50 USP Units/mL) | 5 g | 38 | 42 | Isotonic

For the above Heparin Sodium products the pH range is 5.7 (5.0 to 6.0) and the osmolarity mOsmol/liter (calc.) is 304. Store at 20°C to 25°C (68°F to 77°F). [See USP Controlled Room Temperature.] Protect from freezing.

17 PATIENT COUNSELING INFORMATION

Hemorrhage

Inform patients that it may take them longer than usual to stop bleeding, that they may bruise and/or bleed more easily when they are treated with heparin, and that they should report any unusual bleeding or bruising to their physician. Hemorrhage can occur at virtually any site in patients receiving heparin. Fatal hemorrhages have occurred [see Warnings and Precautions (5.2)].

Prior to Surgery

Advise patients to inform physicians and dentists that they are receiving heparin before any surgery is scheduled [see Warnings and Precautions (5.2)].

Heparin-Induced Thrombocytopenia

Inform patients of the risk of heparin-induced thrombocytopenia (HIT). HIT may progress to the development of venous and arterial thromboses, a condition known as heparin-induced thrombocytopenia and thrombosis (HITT). HIT or HITT can occur up to several weeks after the discontinuation of heparin therapy [see Warnings and Precautions (5.3, 5.4)].

Hypersensitivity

Inform patients that generalized hypersensitivity reactions have been reported. Necrosis of the skin has been reported at the site of subcutaneous injection of heparin [see Warnings and Precautions (5.7), Adverse Reactions (6)].

Other Medications

Because of the risk of hemorrhage, advise patients to inform their physicians and dentists of all medications they are taking, including non-prescription medications, and before starting any new medication [see Drug Interactions (7.2)].

This product’s labeling may have been updated. For the most recent prescribing information, please visit www.pfizer.com.

For medical information about Heparin Sodium in 5% Dextrose Injection, please visit www.pfizermedinfo.com or call 1-800-438‑1985.

Distributed by Hospira, Inc., Lake Forest, IL 60045 USA

LAB-0914-3.0

PRINCIPAL DISPLAY PANEL - 250 mL Bag Label - IM-5191

250 mL SINGLE-DOSE CONTAINER
NDC 0409-7793-52

HEPARIN

25,000 USP Units/250 mL
(100 USP Units/mL)

HEPARIN SODIUM IN
5% DEXTROSE INJECTION

WARNING: CONTAINS SULFITES
EACH 100 mL CONTAINS
HEPARIN SODIUM 10,000 USP
UNITS (PORCINE INTESTINAL
MUCOSA); DEXTROSE, HYDROUS
5 g; CITRIC ACID, ANHYDROUS
51 mg; SODIUM CITRATE,
DIHYDRATE 334 mg; SODIUM
METABISULFITE 20 mg;
STERILE. NOT MADE WITH
NATURAL RUBBER LATEX.
RECOMMENDED DOSAGE:
SEE PRESCRIBING INFORMATION.
ADDITIVES SHOULD NOT
BE MADE TO THIS SOLUTION.
SINGLE DOSE CONTAINER.
DISCARD UNUSED PORTION.
FOR INTRAVENOUS USE ONLY.

Rx ONLY

7
OTHER

DIST. BY HOSPIRA, INC.,
LAKE FOREST, IL 60045 USA
IM-5191
Hospira

PRINCIPAL DISPLAY PANEL - 100 mL Bag Label - IM-3956

100 mL SINGLE-DOSE CONTAINER
NDC 0409-7793-13

HEPARIN

Rx ONLY

10,000 USP Units/100 mL
(100 USP Units/mL)

HEPARIN SODIUM IN
5% DEXTROSE INJECTION
WARNING: CONTAINS SULFITES

EACH 100 mL CONTAINS HEPARIN SODIUM
10,000 USP UNITS (PORCINE INTESTINAL
MUCOSA); DEXTROSE, HYDROUS 5 g; CITRIC
ACID, ANHYDROUS 51 mg; SODIUM CITRATE,
DIHYDRATE 334 mg; SODIUM METABISULFITE
20 mg; STERILE. NOT MADE WITH NATURAL
RUBBER LATEX. USUAL DOSAGE: SEE INSERT.
ADDITIVES SHOULD NOT BE MADE TO THIS
SOLUTION. SINGLE DOSE CONTAINER.
DISCARD UNUSED PORTION.
FOR INTRAVENOUS USE ONLY.

IM - 3956

HOSPIRA, INC.
LAKE FOREST, IL 60045 USA

7
OTHER

Hospira

PRINCIPAL DISPLAY PANEL - 100 mL Bag Label - WR-0482

TO OPEN – TEAR AT NOTCH

100 mL
SINGLE-DOSE
CONTAINER

HEPARIN
10,000 USP Units/100 mL
(100 USP Units/mL)

NDC 0409-7793-13

HEPARIN SODIUM
IN 5% DEXTROSE INJECTION

WARNING: CONTAINS SULFITES

Each 100 mL contains heparin sodium 10,000 USP Units
(porcine intestinal mucosa); dextrose, hydrous 5 g; citric acid,
anhydrous 51 mg; sodium citrate, dihydrate 334 mg; sodium
metabisulfite 20 mg; Sterile. Not made with natural rubber
latex. Usual Dosage: See insert. Store at 20 to 25°C (68 to 77°F).
[See USP Controlled Room Temperature.]

ADDITIVES SHOULD NOT BE MADE TO THIS SOLUTION.

Single Dose Container. Discard Unused Portion. For Intravenous
Use Only.

Rx only

7
OTHER

F WR-0482

Hospira, Inc., Lake Forest, IL 60045 USA
Hospira

PRINCIPAL DISPLAY PANEL - 250 mL Bag Label - IM-5192

250 mL SINGLE-DOSE CONTAINER
NDC 0409-7794-52

HEPARIN

Rx ONLY

12,500 USP Units/250 mL
(50 USP Units/mL)

HEPARIN SODIUM IN
5% DEXTROSE INJECTION

WARNING: CONTAINS SULFITES
EACH 100 mL CONTAINS
HEPARIN SODIUM 5,000 USP
UNITS (PORCINE INTESTINAL
MUCOSA); DEXTROSE,
HYDROUS 5 g; CITRIC ACID,
ANHYDROUS 51 mg; SODIUM
CITRATE, DIHYDRATE 334 mg;
SODIUM METABISULFITE 20 mg;
STERILE. NOT MADE
WITH NATURAL RUBBER LATEX.
RECOMMENDED DOSAGE:
SEE PRESCRIBING INFORMATION.
ADDITIVES SHOULD
NOT BE MADE TO THIS
SOLUTION. SINGLE
DOSE CONTAINER. DISCARD
UNUSED PORTION. FOR
INTRAVENOUS USE ONLY.

7
OTHER

DIST. BY HOSPIRA, INC.,
LAKE FOREST, IL 60045 USA
IM-5192
Hospira

PRINCIPAL DISPLAY PANEL - 250 mL Bag Label – 12135-04

250 mL
NDC 0409-4520-02

Heparin

25,000 USP Units/250 mL
(100 USP Units/mL)

Heparin Sodium
in 5% Dextrose Injection

Warning: contains sulfites
Each 100 mL contains Heparin Sodium 10,000 USP units
(Porcine Intestinal Mucosa); Dextrose, Hydrous 5 g; Citric Acid,
Anhydrous 51 mg; Sodium Citrate, Dihydrate 334 mg;
Sodium Metabisulfite 20 mg; Sterile. Not made with natural
rubber latex. Recommended dosage: See prescribing information.
Additives should not be made to this solution.
Single dose container. Discard unused portion.
Inspect bag by squeezing firmly. If leaks are found, discard.
Store at 20°C to 25°C (68°F to 77°F). [See USP Controlled Room
Temperature.] Protect from freezing.
For Intravenous Use only. Do not remove from overwrap until
ready for use.

Rx ONLY

5
PP

Distributed by Hospira, Inc.,
Lake Forest, IL 60045 USA
12135-04
Hospira